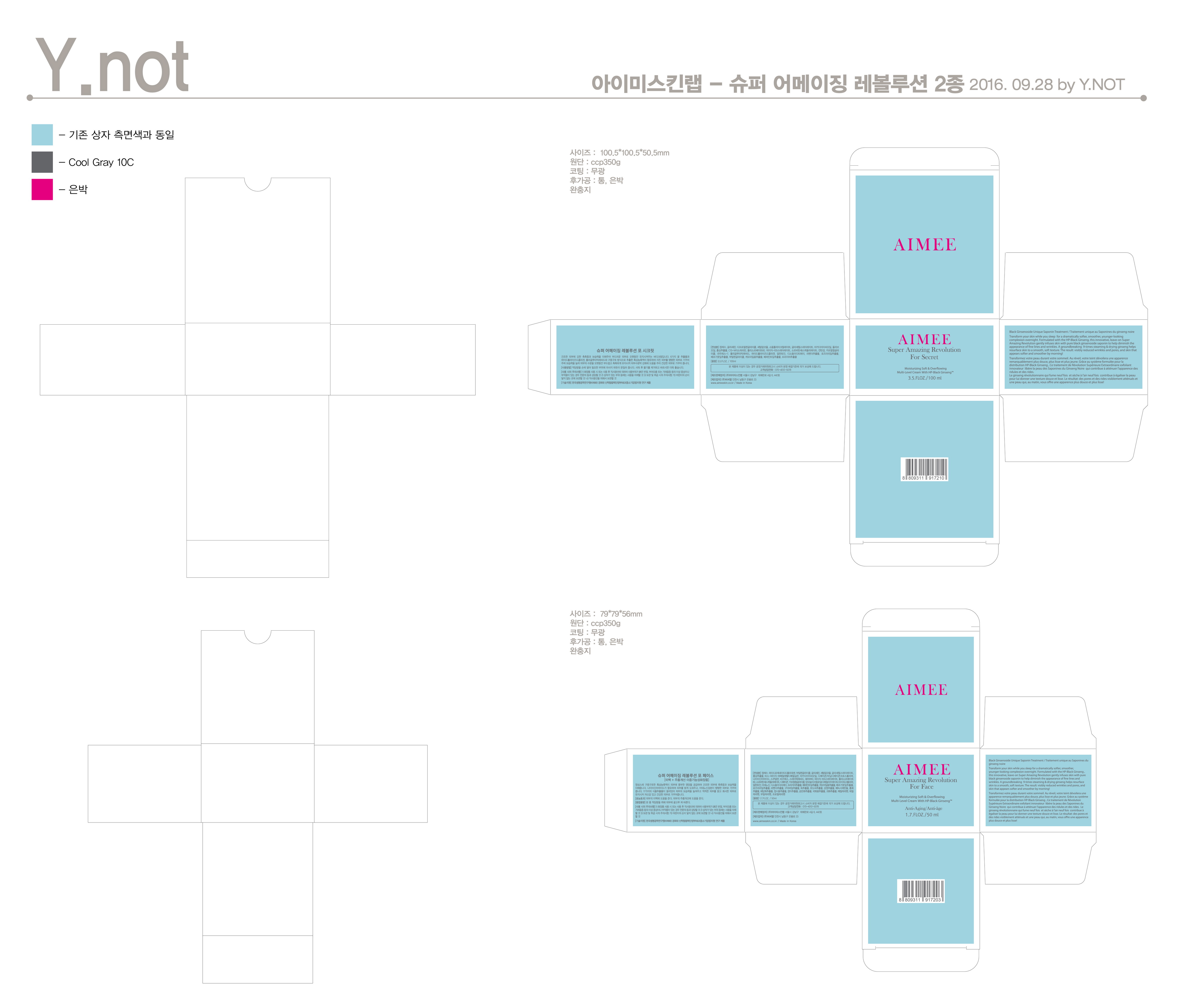 DRUG LABEL: Super Amazing Revolution For Face
NDC: 71711-0002 | Form: CREAM
Manufacturer: Aimeeskinlab Co., Ltd.
Category: otc | Type: HUMAN OTC DRUG LABEL
Date: 20211008

ACTIVE INGREDIENTS: ADENOSINE 0.04 g/100 mL; NIACINAMIDE 2 g/100 mL
INACTIVE INGREDIENTS: WATER; GLYCERIN

Drug Facts

ACTIVE INGREDIENT

Niacinamide, Adenosine

INACTIVE INGREDIENT

Water, Butylene Glycol, Glycerin, Panax Ginseng Root, etc.

PURPOSE

Skin Protectant - Anti-wrinkle & Whitening care

keep out of reach of the children

INDICATIONS AND USAGE

Apply a proper amount on the skin and spread evenly.

WARNINGS

For external use only.
Avoid contact with eyes. Not for human consumption.
Discontinue use if irritation occurs.
If irritation persists, consult a physician.

DOSAGE AND ADMINISTRATION

for external use only